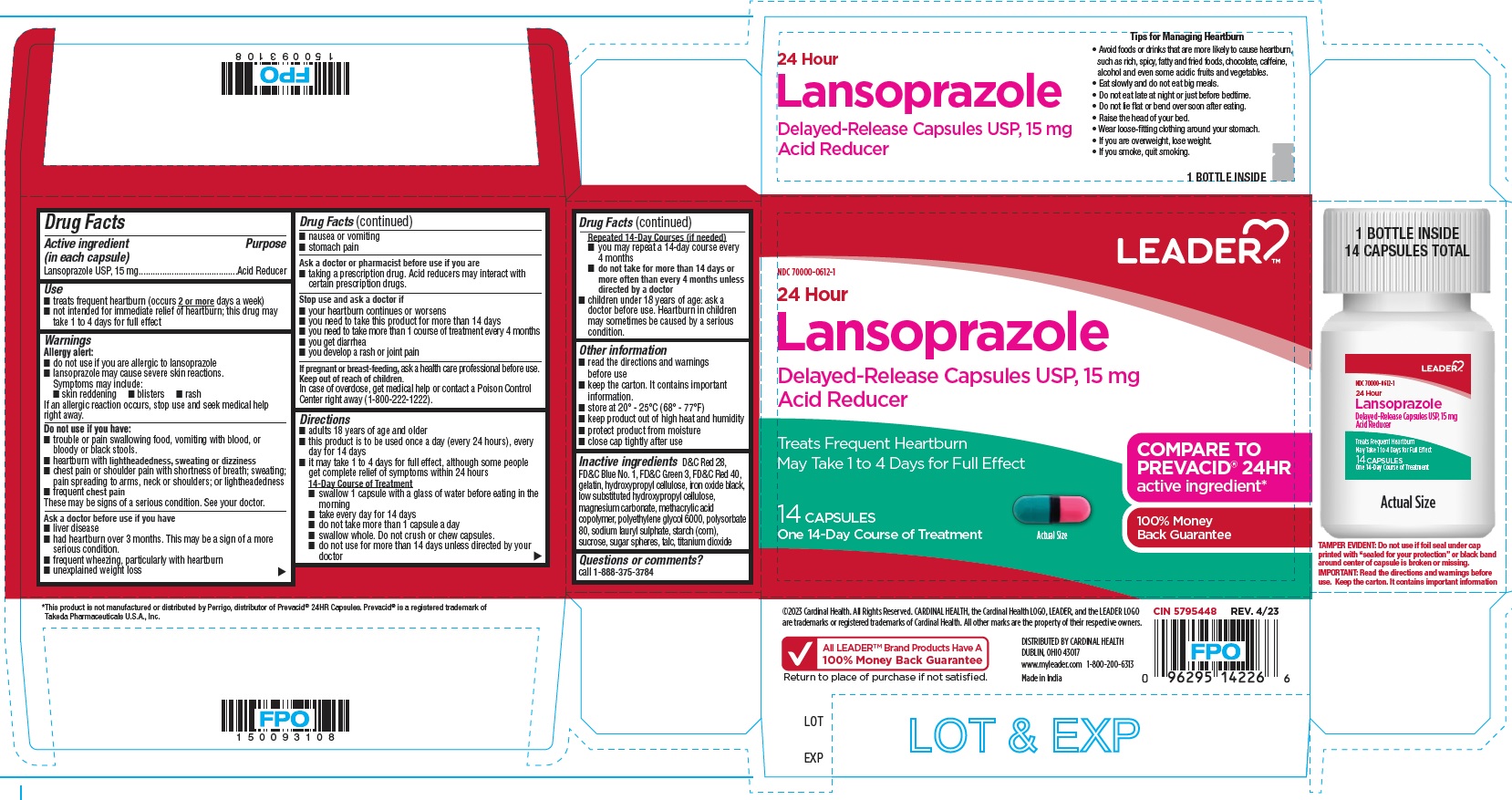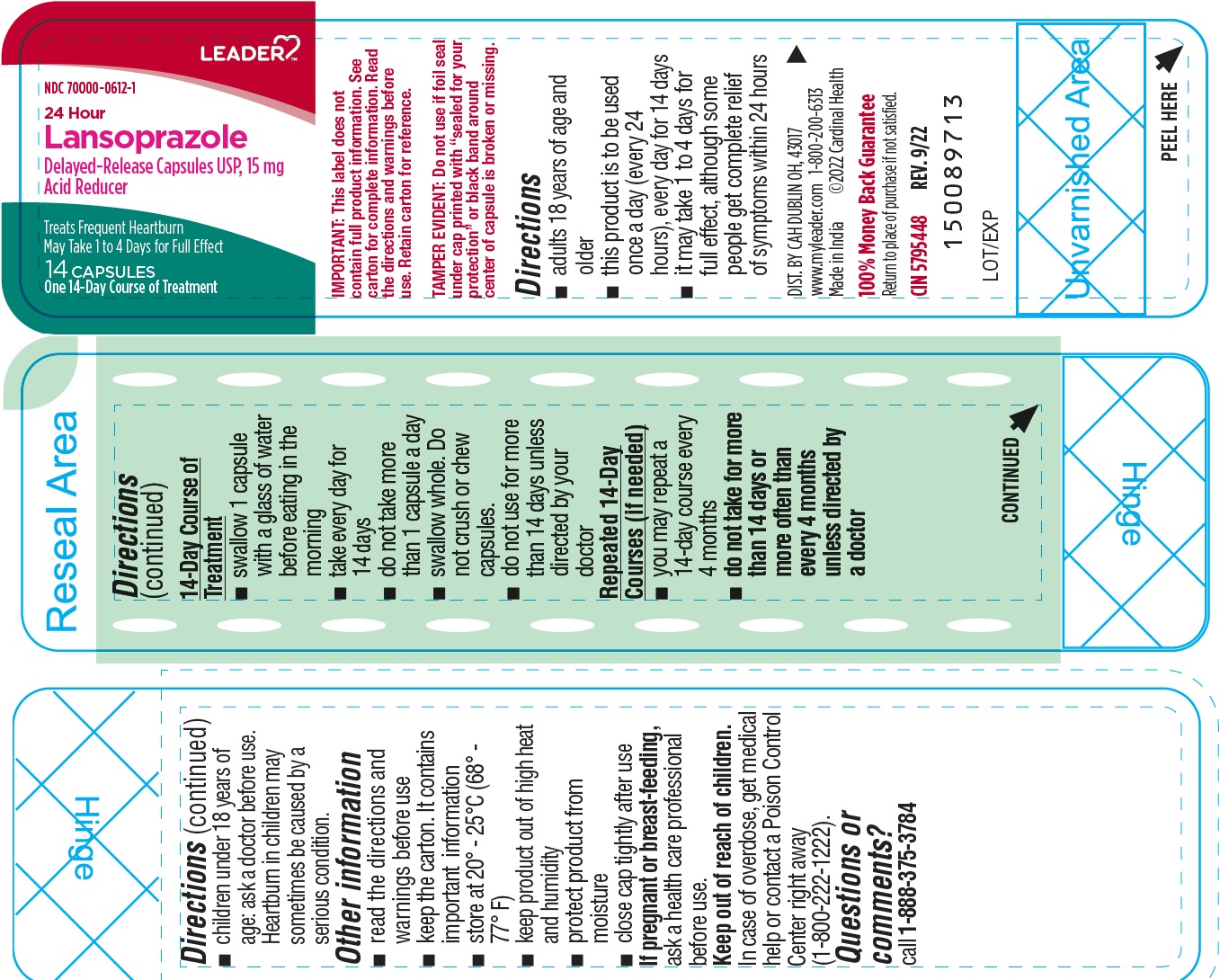 DRUG LABEL: Lansoprazole
NDC: 70000-0612 | Form: CAPSULE, DELAYED RELEASE
Manufacturer: LEADER/ Cardinal Health 110, Inc.
Category: otc | Type: HUMAN OTC DRUG LABEL
Date: 20250727

ACTIVE INGREDIENTS: Lansoprazole 15 mg/1 1
INACTIVE INGREDIENTS: D&C RED NO. 28; FD&C BLUE NO. 1; FD&C GREEN NO. 3; FD&C RED NO. 40; GELATIN; HYDROXYPROPYL CELLULOSE, UNSPECIFIED; FERROSOFERRIC OXIDE; LOW-SUBSTITUTED HYDROXYPROPYL CELLULOSE, UNSPECIFIED; MAGNESIUM CARBONATE; METHACRYLIC ACID AND ETHYL ACRYLATE COPOLYMER; POLYETHYLENE GLYCOL 6000; POLYSORBATE 80; SODIUM LAURYL SULFATE; STARCH, CORN; SUCROSE; TALC; TITANIUM DIOXIDE

Lansoprazole Delayed Release Capsules USP

Active ingredient (in each capsule)

Lansoprazole USP, 15 mg

Purpose

Acid reducer

Use

- treats frequent heartburn (occurs 2 or more days a week)
- not intended for immediate relief of heartburn; this drug may take 1 to 4 days for full effect

Warnings

Allergy alert:

- do not use if you are allergic to lansoprazole
- lansoprazole may cause severe skin reactions.

Symptoms may include:

- skin reddening
- blisters
- rash

If an allergic reaction occurs, stop use and seek medical help right away.

Do not use if you have:

- trouble or pain swallowing food, vomiting with blood, or bloody or black stools.
- heartburn with lightheadedness, sweating or dizziness
- chest pain or shoulder pain with shortness of breath; sweating; pain spreading to arms, neck or shoulders; or lightheadedness
- frequent chest pain
  These may be signs of a serious condition. See your doctor

Ask a doctor before use if you have

- liver disease
- had heartburn over 3 months. This may be a sign of a more serious condition.
- frequent wheezing, particularly with heartburn
- unexplained weight loss
- nausea or vomiting
- stomach pain

Ask a doctor or pharmacist before use if you are

- taking a prescription drug. Acid reducers may interact with certain prescription drugs.

Stop use and ask a doctor if

- your heartburn continues or worsens
- you need to take this product for more than 14 days
- you need to take more than 1 course of treatment every 4 months
- you get diarrhea
- you develop a rash or joint pain

If pregnant or breast-feeding,

ask a healthcare professional before use.

Keep out of reach of children.

In case of overdose, get medical help or contact a Poison Control Center right away (1-800-222-1222).

Directions

- adults 18 years of age and older
- this product is to be used once a day (every 24 hours), every day for 14 days
- it may take 1 to 4 days for full effect, although some people get complete relief of symptoms within 24 hours

14-Day Course of Treatment

- swallow 1 capsule with a glass of water before eating in the morning
- take every day for 14 days
- do not take more than 1 capsule a day
- swallow whole. Do not crush or chew capsules.
- do not use for more than 14 days unless directed by your doctor

Repeated 14-Day Courses (if needed)

- you may repeat a 14-day course every 4 months
- do not take for more than 14 days or more often than every 4 months unless directed by a doctor
- children under 18 years of age: ask a doctor before use. Heartburn in children may sometimes be caused by a serious condition.

Other information

- read the directions and warnings before use
- keep the carton. It contains important information.
- store at 20 – 25°C (68° – 77° F)
- keep product out of high heat and humidity
- protect product from moisture
- close cap tightly after use

Inactive ingredients

D&C Red 28, FD&C Blue No.1, FD&C Green 3, FD&C Red 40, gelatin, hydroxypropyl cellulose, iron oxide black, low substituted hydroxypropyl cellulose, magnesium carbonate, methacrylic acid copolymer, polyethylene glycol 6000, polysorbate 80, sodium lauryl sulphate, starch (corn), sucrose, sugar spheres, talc, titanium dioxide

Questions or comments?

call 1-888-375-3784

Tips For Managing Heartburn

• Avoid foods or drinks that are more likely to cause heartburn, such as rich, spicy, fatty and fried foods, chocolate, caffeine, alcohol and even some acidic fruits and vegetables.

• Eat slowly and do not eat big meals.

• Do not eat late at night or just before bedtime.

• Do not lie flat or bend over soon after eating.

• Raise the head of your bed.

• Wear loose-fitting clothing around your stomach.

• If you are overweight, lose weight.

• If you smoke, quit smoking.

PRINCIPAL DISPLAY PANEL- Carton Label

Lansoprazole Delayed- Release Capsules USP, 15 mg